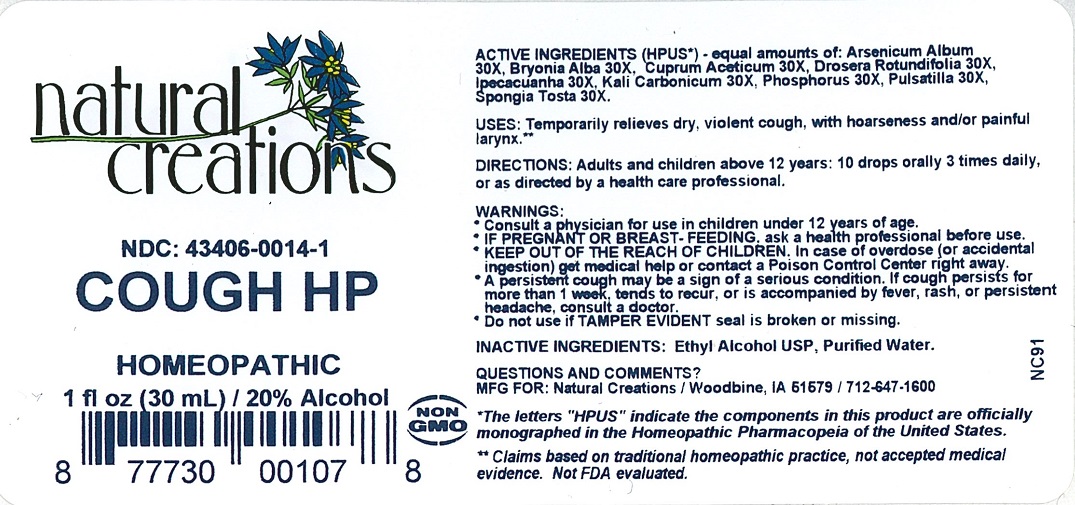 DRUG LABEL: Cough HP
NDC: 43406-0014 | Form: LIQUID
Manufacturer: Natural Creations, Inc
Category: homeopathic | Type: HUMAN OTC DRUG LABEL
Date: 20221123

ACTIVE INGREDIENTS: ARSENIC TRIOXIDE 30 [hp_X]/1 mL; BRYONIA ALBA ROOT 30 [hp_X]/1 mL; CUPRIC ACETATE 30 [hp_X]/1 mL; DROSERA ROTUNDIFOLIA 30 [hp_X]/1 mL; IPECAC 30 [hp_X]/1 mL; POTASSIUM CARBONATE 30 [hp_X]/1 mL; PHOSPHORUS 30 [hp_X]/1 mL; PULSATILLA VULGARIS 30 [hp_X]/1 mL; SPONGIA OFFICINALIS SKELETON, ROASTED 30 [hp_X]/1 mL
INACTIVE INGREDIENTS: ALCOHOL; WATER

Cough HP

ACTIVE INGREDIENT

ACTIVE INGREDIENTS (HPUS*) - equal amounts of: Arsenicum Album 30X, Bryonia Alba 30X, Cuprum Aceticum 30X, Drosera Rotundifolia 30X, Ipecacuanha 30X, Kali Carbonicum 30X, Phosphorus 30X, Pulsatilla 30X, Spongia Tosta 30X.

INDICATIONS AND USAGE

USES: Temporarily relieves dry, violent cough, with hoarseness and/or painful larynx.**

PURPOSE

USES: Temporarily relieves dry, violent cough, with hoarseness and/or painful larynx.**

DOSAGE AND ADMINISTRATION

DIRECTIONS: Adults and children above 12 years: 10 drops orally 3 times daily, or as directed by a health care professional.

KEEP OUT OF REACH OF CHILDREN

KEEP OUT OF THE REACH OF CHILDREN. In case of overdose (or accidental ingestion) get medical help or contact a Poison Control Center right away.

WARNINGS:

- Consult a physician for use in children under 12 years of age.
- IF PREGNANT OR BREAST-FEEDING, ask a health care professional before use.
- KEEP OUT OF THE REACH OF CHILDREN. In case of overdose (or accidental ingestion) get medical help or contact a Poison Control Center right away.
- A persistant cough may be a sign of a serious condition. If cough persists for more than 1 week, tends to recur or is accompanied by fever, rash, or persistent headache, consult a doctor.
- Do not use if TAMPER EVIDENT seal is broken or missing.

INACTIVE INGREDIENTS: Ethyl Alcohol USP, Purified Water.

QUESTIONS & COMMENTS?

Natural Creations, Inc. / Woodbine, IA 51579 / 712-647-1600

REFERENCES

* The letters "HPUS" indicate the components in the product are officially monographed in the Homeopathic Pharmacopeia of the United States.

**Claims based on traditional homeopathic practice, not accepted medical evidence. Not FDA evaluated.

PACKAGE LABEL

NDC: 43406-0014-1

Cough HP

HOMEOPATHIC

1 fl oz (30mL) / 20% Alcohol